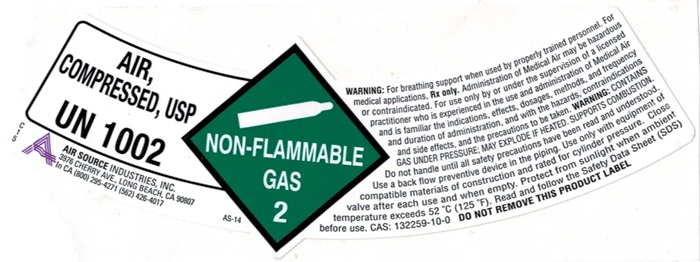 DRUG LABEL: AIR COMPRESSED
                
NDC: 10167-600 | Form: GAS
Manufacturer: Air Source Industries
Category: prescription | Type: HUMAN PRESCRIPTION DRUG LABEL
Date: 20241006

ACTIVE INGREDIENTS: OXYGEN 20 L/100 L
INACTIVE INGREDIENTS: NITROGEN

AIR COMPRESSED Product Label

AIR COMPRESSED USP UN 1002

C15 A AIR SOURCE INDUSTRIES, INC.

3976 CHERRY AVE., LONG BEACH, CA 90807

In CA (800) 295-4271 (562) 426-4017

NON-FLAMMABLE GAS @ AS-14

WARNING: For breathing support when used by properly trained personnel. For medical applications. Rx only. Administration of Medical Air may be hazardous or contraindicated. For use only by or under the supervision of a licensed practitioner who is experienced in the use and administration of Medical Air and is familiar the indications, effects, dosages, methods, and frequency and duration of administration, and with the hazards, contraindications and side effects, and the precautions to be taken. WARNING: CONTAINS GAS UNDER PRESSURE; MAY EXPLODE IF HEATED. SUPPORTS COMBUSTION. Do not handle until all safety precautions have been read and understood. Use a back flow preventive device in the piping. Use only with equipment of compatible materials of construction and rated for cylinder pressure. Close valve after each use and when empty. Protect from sunlight when ambient temperature exceeds 52°C (125°F). Read and follow the Safety Data Sheet (SDS) before use. CAS 132259-10-0 DO NOT REMOVE THIS PRODUCT LABEL